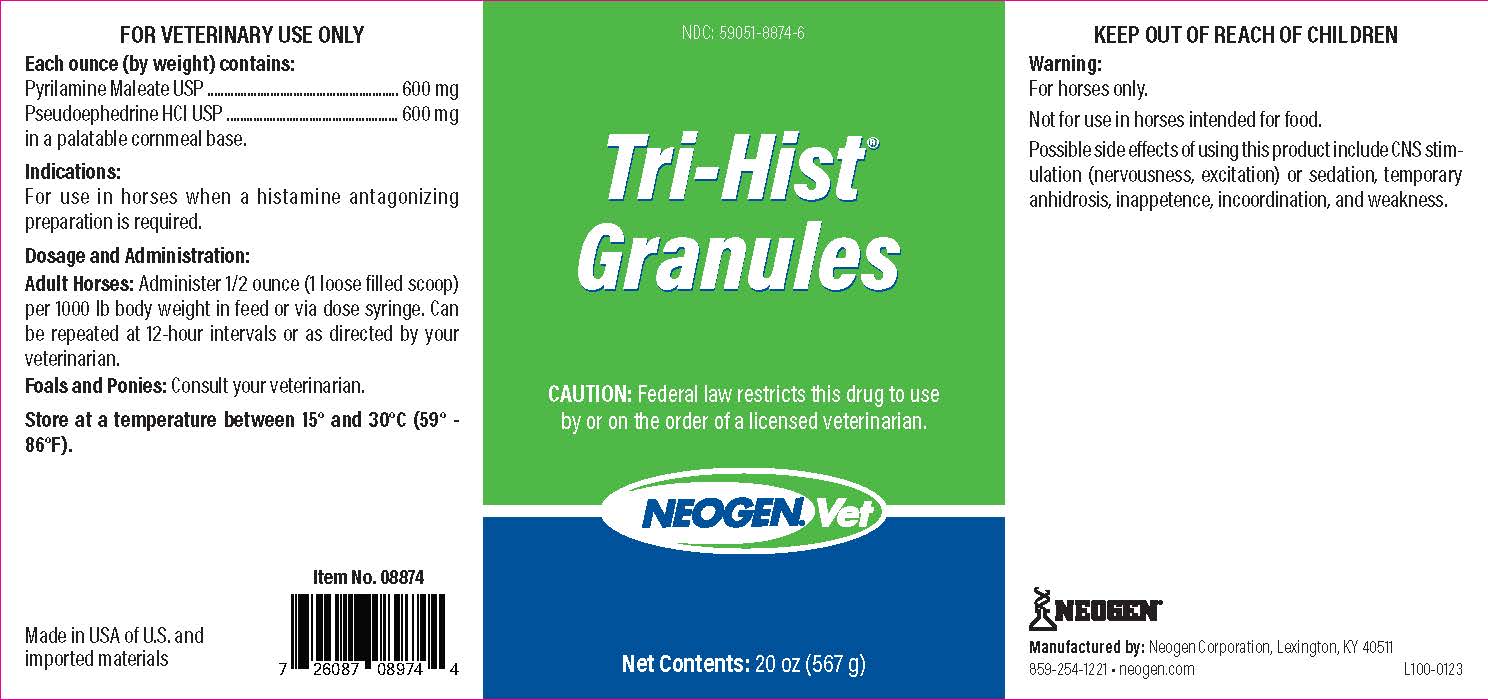 DRUG LABEL: Tri-Hist Granules
NDC: 59051-8874 | Form: GRANULE
Manufacturer: Neogen Corporation-Mercer Rd
Category: animal | Type: PRESCRIPTION ANIMAL DRUG LABEL
Date: 20240102

ACTIVE INGREDIENTS: PSEUDOEPHEDRINE HYDROCHLORIDE 600 mg/28.35 g; PYRILAMINE MALEATE 600 mg/28.35 g
INACTIVE INGREDIENTS: CORN GRAIN

Tri-Hist Granules

KEEP OUT OF REACH OF CHILDREN

Warning:

For horses only.

Not for use in horses intended for food.

Possible side effects of using this product include CNS stimulation (nervousness, excitation) or sedation, temporary anhidrosis, inappetance, incoordination, and weakness.

WARNINGS

FOR VETERINARY USE ONLY

Indications:

For use in horses when a histamine antagonizing preparation is required.

Dosage and Administration:

Adult Horses: Administer 1/2 ounce (1 loose filled scoop) per 1000 lb body weight in feed or via dose syringe. Can be repeated at 12-hour intervals or as directed by your veterinarian.

Foals and Ponies: Consult your veterinarian.

STORAGE AND HANDLING

Store at a temperature between 15° and 30°C (59° - 86°F).

Manufactured by: Neogen Corporation, Lexington, KY 40511

859-254-1221 • neogen.com L100-0123

Principal Display Panel - 20oz

NDC: 59051-8874-6

Tri-Hist®

Granules

CAUTION: Federal law restricts this drug to use by or on the order of a licensed veterinarian.

NEOGENVet

Net Contents: 20 oz (567 g)